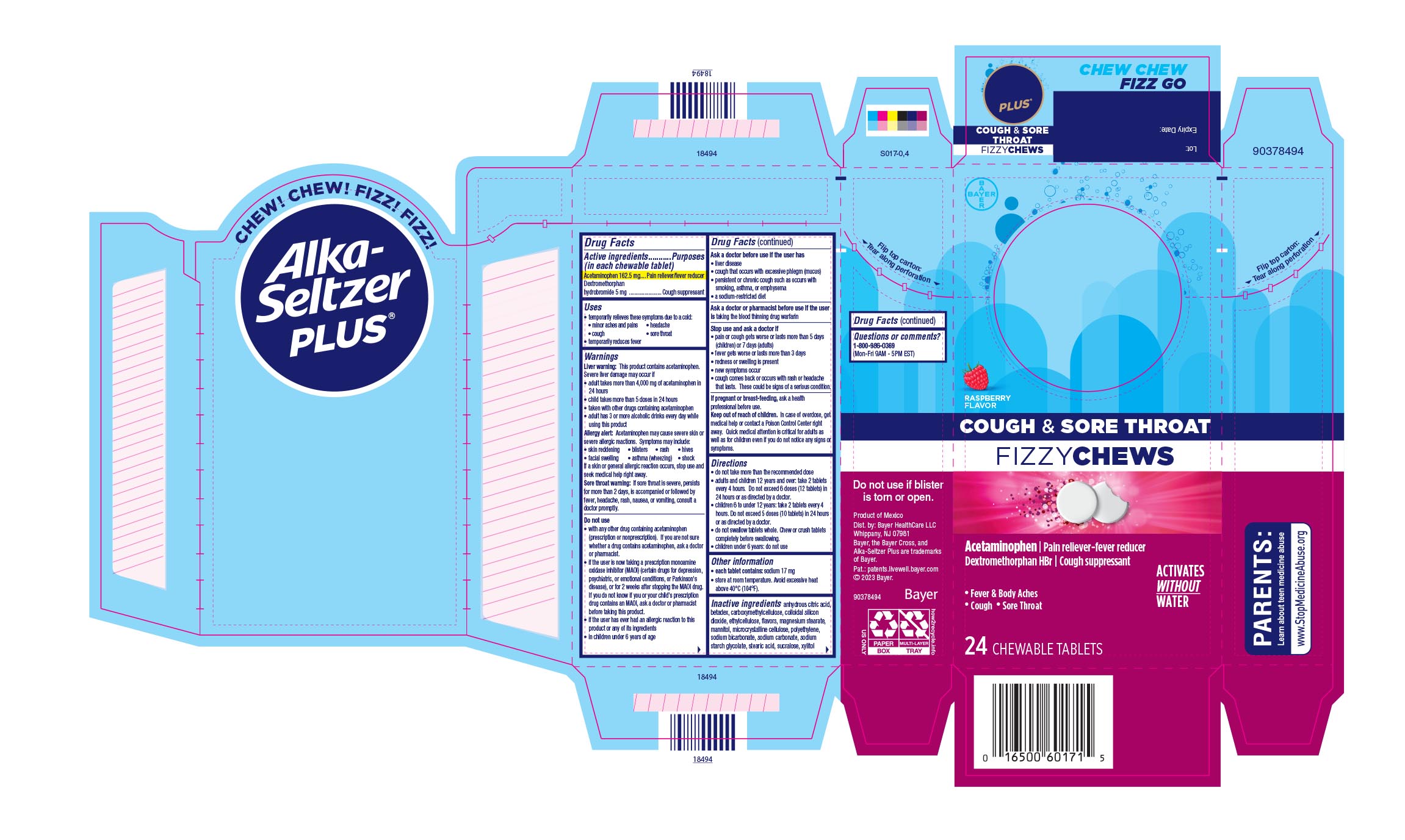 DRUG LABEL: Alka-Seltzer Plus Cough and Sore Throat FizzyChews
NDC: 0280-0152 | Form: TABLET, CHEWABLE
Manufacturer: Bayer HealthCare LLC.
Category: otc | Type: HUMAN OTC DRUG LABEL
Date: 20251204

ACTIVE INGREDIENTS: DEXTROMETHORPHAN HYDROBROMIDE 5 mg/1 1; ACETAMINOPHEN 162.5 mg/1 1
INACTIVE INGREDIENTS: STEARIC ACID; MAGNESIUM STEARATE; MANNITOL; ANHYDROUS CITRIC ACID; SUCRALOSE; SODIUM BICARBONATE; CELLULOSE, MICROCRYSTALLINE; SILICON DIOXIDE; XYLITOL; BETADEX; SODIUM STARCH GLYCOLATE TYPE A

Alka-Seltzer Plus Cough and Sore Throat FizzyChews UI 1615059

Drug Facts

Active ingredients (in each tablet) Purposes

Acetaminophen 162.5 mg…………….………...Pain reliever/fever reducer

Dextromethorphan hydrobromide 5 mg…….....………Cough suppressant

Uses

· temporarily relieves these symptoms due to a cold:

· minor aches and pains · headache

· cough · sore throat

· temporarily reduces fever

Warnings

Liver warning: This product contains acetaminophen. Severe liver damage may occur if

· adult takes more than 4,000 mg of acetaminophen in 24 hours

· child takes more than 5 doses in 24hours

· taken with other drugs containing acetaminophen

· adult has 3 or more alcoholic drinks every day while using this product

Allergy alert: Acetaminophen may cause severe skin or severe

allergic reactions. Symptoms may include:

· skin reddening · blisters · rash · hives

· facial swelling · asthma (wheezing) · shock

If a skin or general allergic reaction occurs, stop use and seek medical help right away.

Sore throat warning: If sore throat is severe, persists for more than

2 days, is accompanied or followed by fever, headache, rash, nausea,

or vomiting, consult a doctor promptly.

Do not use

● with any other drug containing acetaminophen (prescription or nonprescription). If you are not sure whether a drug contains acetaminophen, ask a doctor or pharmacist.

● if you are now taking a prescription monoamine oxidase inhibitor (MAOI) (certain drugs for depression, psychiatric, or emotional conditions, or Parkinson's disease), or for 2 weeks after stopping the MAOI drug. If you do not know if your prescription drug contains an MAOI, ask a doctor or pharmacist before taking this product.

● if you have ever had an allergic reaction to this product or any of its ingredients

● in children under 6 years of age

Ask a doctor before use if you have

● liver disease

● cough with excessive phlegm (mucus)

● persistent or chronic cough such as occurs with smoking, asthma,

or emphysema

● a sodium restricted diet

Ask a doctor or pharmacist before use if the user is taking the blood thinning drug warfarin

When using this product

● do not exceed recommended dosage

● may cause marked drowsiness

● avoid alcoholic drinks

● alcohol, sedatives, and tranquilizers may increase drowsiness

● be careful when driving a motor vehicle or operating machinery

● excitability may occur, especially in childre

Stop use and ask a doctor if

· pain or cough gets worse or lasts more than 5 days (children) or 7 days (adults)

· fever gets worse or lasts more than 3 days

· redness or swelling is present

· new symptoms occur

· cough comes back or occurs with rash or headache that lasts.

PREGNANCY OR BREAST FEEDING

If pregnant or breast-feeding, ask a health professional before use.

Keep out of reach of children. In case of overdose, get medical help or contact a Poison Control Center right away. Quick medical attention is critical for adults as well as for children even if you do not notice any signs or symptoms

Directions

· do not take more than the recommended dose

· adults and children 12 years and over: take 2 tablets every 4 hours.

Do not exceed 6 doses (12 tablets) tablets in 24 hours or as directed by a

doctor.

· children 6 to under 12 years: take 2 tablets every 4 hours. Do not

exceed 5 doses (10 tablets) in 24 hours or as directed by a doctor.

· do not swallow tablets whole. Chew or crush tablets completely

before swallowing.

· children under 12 years: do not use

Other information

● each tablet contains: sodium 17 mg

● store at room temperature. Avoid excessive heat above 40o C

(104o F)

Inactive ingredients anhydrous citric acid, betadex,

carboxymethylcellulose, colloidal silicon dioxide, ethylcellulose, flavors,

magnesium stearate, mannitol, microcrystalline cellulose, polyethylene,

sodium bicarbonate, sodium carbonate, sodium starch glycolate, stearic

acid, sucralose, xylitol

Questions or comments? 1-800-986-0369 (Mon-Fri 9AM - 5PM EST)

PACKAGE LABEL

Alka-Seltzer® PLUS

Cough & Sore Throat FIZZY CHEWS

ACETAMINOPHEN/Pain Reliever-Fever Reducer

Dextromethorphan HBr/ Cough Supressant

- Fever & Body Ache
- Cough
- Sore Throat

ACTIVATES WITHOUT WATER

24 CHEWABLE TABLETS